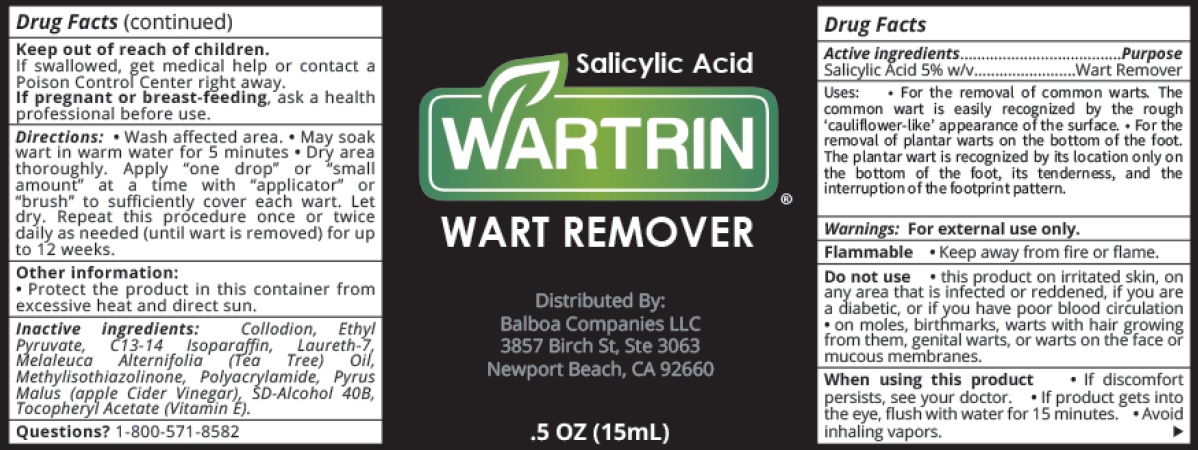 DRUG LABEL: WARTRIN Wart Remover
NDC: 82266-237 | Form: CREAM
Manufacturer: BALBOA COMPANIES LLC
Category: otc | Type: HUMAN OTC DRUG LABEL
Date: 20231111

ACTIVE INGREDIENTS: SALICYLIC ACID 50 mg/1 mL
INACTIVE INGREDIENTS: LYTTA VESICATORIA; ETHYL PYRUVATE; C13-14 ISOPARAFFIN; LAURETH-7; MELALEUCA ALTERNIFOLIA LEAF; METHYLISOTHIAZOLINONE; APPLE CIDER VINEGAR; .ALPHA.-TOCOPHEROL ACETATE

WARTRIN Wart Remover

Active ingredients

Salicylic Acid 5% w/v

Purpose

Wart Remover

Uses:

- For the removal of common warts. The common wart is easily recognized by the rough 'cauliflower-like' appearance of the surface.
- For the removal of plantar warts on the bottom of the foot. The plantar wart is recognized by its location only on the bottom of the foot, its tenderness, and the interruption of the footprint pattern.

Warnings:

For external use only.

Keep away from fire or flame. Flammable •

Do not use

- this product on irritated skin, on any area that is infected or reddened, if you are a diabetic, or if you have poor blood circulation
- on moles, birthmarks, warts with hair growing from them, genital warts, or warts on the face or mucous membranes.

When using this product

- If discomfort persists, see your doctor.
- If product gets into the eye, flush with water for 15 minutes.
- Avoid inhaling vapors.

Keep out of reach of children.

If swallowed, get medical help or contact a Poison Control Center right away.

If pregnant or breast-feeding,

ask a health professional before use.

Directions:

- Wash affected area.
- May soak wart in warm water for 5 minutes
- Dry area thoroughly. Apply "one drop" or "small amount" at a time with "applicator" or "brush" to sufficiently cover each wart. Let dry. Repeat this procedure once or twice daily as needed (until wart is removed) for up to 12 weeks.

Other information:

- Protect the product in this container from excessive heat and direct sun.

Inactive ingredients:

Collodion, Ethyl Pyruvate, C13-14 Isoparaffin, Laureth-7, Melaleuca Alternifolia (Tea Tree) Oil, Methylisothiazolinone, Polyacrylamide, Pyrus Malus (apple Cider Vinegar), SD-Alcohol 40B, Tocopheryl Acetate (Vitamin E).

Questions?

1-800-571-8582